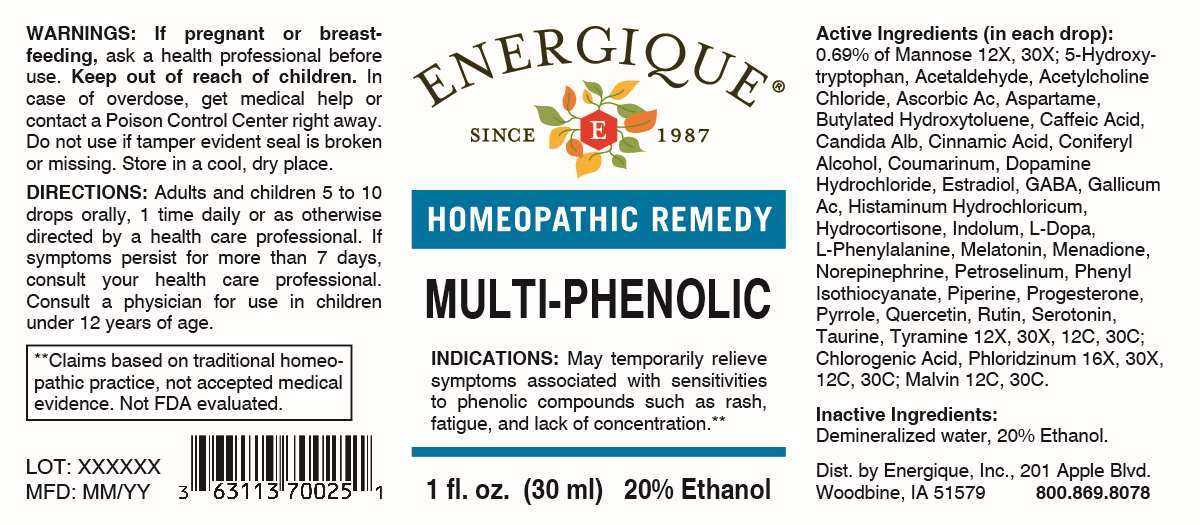 DRUG LABEL: Multi-Phenolic
NDC: 44911-0649 | Form: LIQUID
Manufacturer: Energique, Inc.
Category: homeopathic | Type: HUMAN OTC DRUG LABEL
Date: 20240823

ACTIVE INGREDIENTS: MANNOSE, D- 12 [hp_X]/1 mL; OXITRIPTAN 12 [hp_X]/1 mL; ACETALDEHYDE 12 [hp_X]/1 mL; ACETYLCHOLINE CHLORIDE 12 [hp_X]/1 mL; ASCORBIC ACID 12 [hp_X]/1 mL; ASPARTAME 12 [hp_X]/1 mL; BUTYLATED HYDROXYTOLUENE 12 [hp_X]/1 mL; CAFFEIC ACID 12 [hp_X]/1 mL; CANDIDA ALBICANS 12 [hp_X]/1 mL; CINNAMIC ACID 12 [hp_X]/1 mL; CONIFERYL ALCOHOL 12 [hp_X]/1 mL; COUMARIN 12 [hp_X]/1 mL; DOPAMINE HYDROCHLORIDE 12 [hp_X]/1 mL; ESTRADIOL 12 [hp_X]/1 mL; .GAMMA.-AMINOBUTYRIC ACID 12 [hp_X]/1 mL; GALLIC ACID MONOHYDRATE 12 [hp_X]/1 mL; HISTAMINE DIHYDROCHLORIDE 12 [hp_X]/1 mL; HYDROCORTISONE 12 [hp_X]/1 mL; INDOLE 12 [hp_X]/1 mL; LEVODOPA 12 [hp_X]/1 mL; PHENYLALANINE 12 [hp_X]/1 mL; MELATONIN 12 [hp_X]/1 mL; MENADIONE 12 [hp_X]/1 mL; NOREPINEPHRINE BITARTRATE 12 [hp_X]/1 mL; PETROSELINUM CRISPUM WHOLE 12 [hp_X]/1 mL; PHENYL ISOTHIOCYANATE 12 [hp_X]/1 mL; PIPERINE 12 [hp_X]/1 mL; PROGESTERONE 12 [hp_X]/1 mL; PYRROLE 12 [hp_X]/1 mL; QUERCETIN 12 [hp_X]/1 mL; RUTIN 12 [hp_X]/1 mL; SEROTONIN HYDROCHLORIDE 12 [hp_X]/1 mL; TAURINE 12 [hp_X]/1 mL; TYRAMINE 12 [hp_X]/1 mL; CHLOROGENIC ACID 16 [hp_X]/1 mL; PHLORIZIN 16 [hp_X]/1 mL; MALVIN 12 [hp_C]/1 mL
INACTIVE INGREDIENTS: WATER; ALCOHOL

DRUG FACTS:

ACTIVE INGREDIENTS:

(in each drop): 0.69% of Mannose 12X, 30X; 5-Hydroxytryptophan 12X, 30X, 12C, 30C, Acetaldehyde 12X, 30X, 12C, 30C, Acetylcholine Chloride 12X, 30X, 12C, 30C, Ascorbicum Acidum 12X, 30X, 12C, 30C, Aspartame 12X, 30X, 12C, 30C, Butylated Hydroxytoluene 12X, 30X, 12C, 30C, Caffeic Acid 12X, 30X, 12C, 30C, Candida Albicans 12X, 30X, 12C, 30C, Cinnamic Acid 12X, 30X, 12C, 30C, Coniferyl Alcohol 12X, 30X, 12C, 30C, Coumarinum 12X, 30X, 12C, 30C, Dopamine Hydrochloride 12X, 30X, 12C, 30C, Estradiol 12X, 30X, 12C, 30C, Gaba (Gamma-Aminobutyric Acid) 12X, 30X, 12C, 30C, Gallicum Acidum 12X, 30X, 12C, 30C, Histaminum Hydrochloricum 12X, 30X, 12C, 30C, Hydrocortisone 12X, 30X, 12C, 30C, Indolum 12X, 30X, 12C, 30C, L-Dopa 12X, 30X, 12C, 30C, L-Phenylalanine 12X, 30X, 12C, 30C, Melatonin 12X, 30X, 12C, 30C, Menadione 12X, 30X, 12C, 30C, Norepinephrine (Bitartrate) 12X, 30X, 12C, 30C, Petroselinum Sativum 12X, 30X, 12C, 30C, Phenyl Isothiocyanate 12X, 30X, 12C, 30C, Piperine 12X, 30X, 12C, 30C, Progesterone 12X, 30X, 12C, 30C, Pyrrole 12X, 30X, 12C, 30C, Quercetin 12X, 30X, 12C, 30C, Rutin 12X, 30X, 12C, 30C, Serotonin (Hydrochloride) 12X, 30X, 12C, 30C, Taurine 12X, 30X, 12C, 30C, Tyramine 12X, 30X, 12C, 30C; Chlorogenic Acid 16X, 30X, 12C, 30C, Phloridzinum16X, 30X, 12C, 30C; Malvin 12C, 30C.

PURPOSE:

May temporarily relieve symptoms associated with sensitivities to phenolic compounds such as rash, fatigue, and lack of concentration.**

**Claims based on traditional homeopathic practice, not accepted medical evidence. Not FDA evaluated.

WARNINGS:

If pregnant or breast-feeding, ask a health professional before use.

Keep out of reach of children. In case of overdose, get medical help or contact a Poison Control Center right away.

Do not use if tamper evident seal is broken or missing. Store in a cool, dry place.

KEEP OUT OF REACH OF CHILDREN:

In case of overdose, get medical help or contact a Poison Control Center right away.

DIRECTIONS:

Adults and children 5 to 10 drops orally, 1 time daily or as otherwise directed by a health care professional. If symptoms persist for more than 7 days, consult your health care professional. Consult a physician for use in children under 12 years of age.

INDICATIONS:

May temporarily relieve symptoms associated with sensitivities to phenolic compounds such as rash, fatigue, and lack of concentration.**

**Claims based on traditional homeopathic practice, not accepted medical evidence. Not FDA evaluated.

INACTIVE INGREDIENTS:

Demineralized water, 20% Ethanol.

QUESTIONS:

Dist. by Energique, Inc.

201 Apple Blvd

Woodbine, IA 51579

800.869.8078

PACKAGE LABEL DISPLAY:

ENERGIQUE
SINCE 1987
HOMEOPATHIC REMEDY
MULTI-PHENOLIC
1 fl. oz. (30 ml)